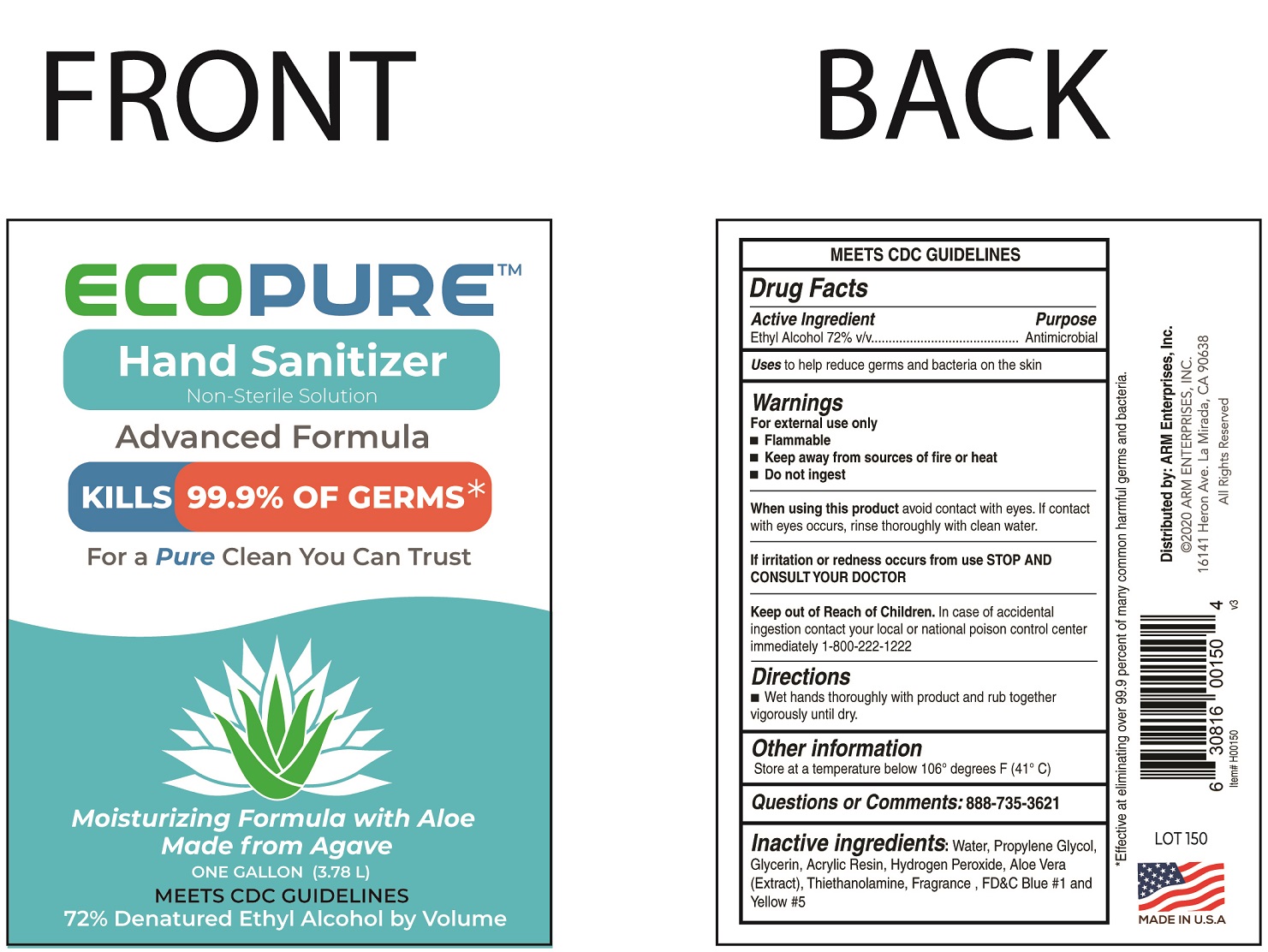 DRUG LABEL: ECOPURE HAND SANITIZER
NDC: 79241-001 | Form: GEL
Manufacturer: Adrian Rivera Maynez Enterprises Inc
Category: otc | Type: HUMAN OTC DRUG LABEL
Date: 20200816

ACTIVE INGREDIENTS: ALCOHOL 0.72 mL/1 mL
INACTIVE INGREDIENTS: WATER; PROPYLENE GLYCOL; GLYCERIN; HYDROGEN PEROXIDE; ALOE VERA LEAF; TROLAMINE; FD&C BLUE NO. 1; FD&C YELLOW NO. 5

ECOPURE HAND SANITIZER

Active Ingredient

Ethyl Alcohol 72% v/v

Purpose

Antimicrobial

Uses

to help reduce germs and bacteria on the skin

Warnings

For external use only

- Flammable
- Keep away from sources of fire or heat
- Do not ingest

When using this product

avoid contact with eyes. If contact with eyes occurs, rinse thoroughly with clean water.

STOP AND CONSULT YOUR DOCTOR

If irritation or redness occurs

Keep out of Reach of Children.

In case of accidental ingestion contact the your local or national poison control center immediately 1-800-222-1222

Directions

- Wet hands thoroughly with product and rub together vigorously until dry.

Other information

Store at a temperature below 106° degrees F (41° C)

Questions or comments:

888-735-3621

Inactive ingredients:

Water, Propylene Glycol, Glycerin, Acrylic Resin, Hydrogen Peroxide, Aloe Vera (Extract), Triethanolamine, Fragrance, FD&C Blue #1 and Yellow #5